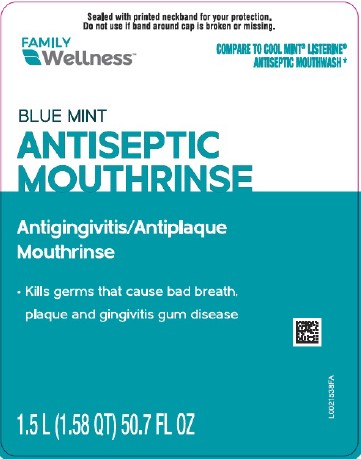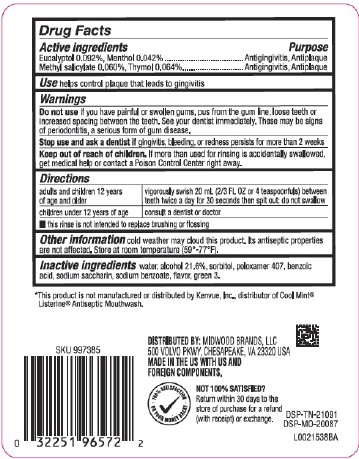 DRUG LABEL: Antispetic
NDC: 55319-664 | Form: MOUTHWASH
Manufacturer: Family Dollar Stores, Inc
Category: otc | Type: HUMAN OTC DRUG LABEL
Date: 20260224

ACTIVE INGREDIENTS: EUCALYPTOL 0.92 mg/1 mL; MENTHOL 0.42 mg/1 mL; METHYL SALICYLATE 0.6 mg/1 mL; THYMOL 0.64 mg/1 mL
INACTIVE INGREDIENTS: WATER; ALCOHOL; SORBITOL; POLOXAMER 407; BENZOIC ACID; SACCHARIN SODIUM; SODIUM BENZOATE; FD&C GREEN NO. 3

Family Wellness 664.003/664AT rev 2 - 664AU
Blue Mint Antiseptic Mouthrinse

Active ingredients

Eucalyptol 0.092%

Menthol 0.042%

Methyl salicylate 0.060%

Thymol 0.064%

Purpose

Antigingivitis, Antiplaque

Use

helps control plaque that leads to gingivitis

Warnings

for this product

Do not use

if you have painful or swollen gums, pus from the gum line, loose teeth or increased spacing between the teeth. See your dentist immediately. These may be signs of periodontitis, a serious form of gum disease.

Stop use and ask a dentist if

gingivitis, bleeding, or redness persists for more than 2 weeks

Keep out of reach of children.

If more than used for rinsing is accidentally swallowed, get medical help or contact a Poison Control Center right away.

Directions

adults and children 12 years of age and older - vigorously swish 20 mL (2/3 FL OZ or 4 teaspoonfuls) between teeth twice a day for 30 seconds then spit out; do not swallow

children under 12 years of age - consult a dentist or doctor

- this rinse is not intended to replace brushing or flossing

Other information

cold weather may cloud this product. Its antiseptic properties are not affected. Store at room temperature (59°-77°F).

Inactive ingredients

water, alcohol 21.6%, sorbitol, poloxamer 407, benzoic acid, sodium saccharin, sodium benzoate, flavor, green 3

Disclaimer

*This product is not manufactured or distributed by Kenvue, Inc., distributor of Cool Mint® Listerine® Antiseptic Mouthwash.

Adverse Reactions

DISTRIBUTED BY: MIDWOOD BRANDS, LLC

500 VOLVO PKWY, CHESAPEAKE, VA 23320 USA

MADE IN THE US WITH US AND FOREIGN COMPONENTS.

100% SATISFACTION OR YOUR MONEY BACK

Not 100% satisfied? Return within 30 days to the store of purchase for a refund (with receipt) or exchange.

DSP-TN-21091

DSP-MO-20087

Principle Panel Display

Sealed with printed neckband for your protection.

Do not use if band around cap is broken or missing.

FAMILY WELLNESS™

COMPARE TO COOL MINT® LISTERINE® ANTISEPTIC MOUTWASH*

BLUE MINT

ANTISEPTIC MOUTHRINSE

Antigingivitis/Antiplaque Mouthrinse

- Kills germs that cause bad breath, plaque and disease gingivitis gum disease

1.5 L (1.58 QT) 50.7 FL OZ